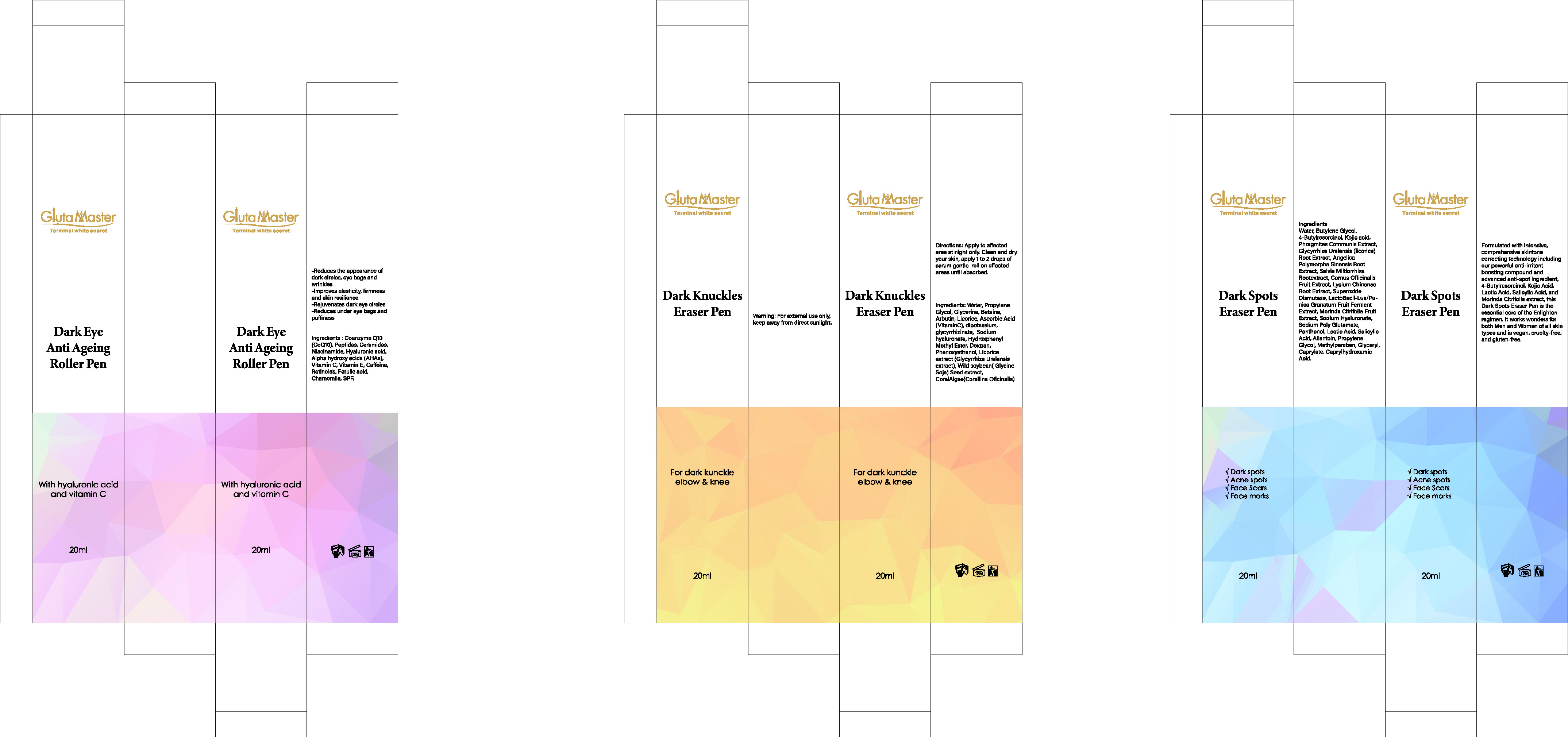 DRUG LABEL: Dark Eye Anti Ageing Roller Pen
NDC: 84423-085 | Form: LOTION, AUGMENTED
Manufacturer: Guangzhou Kadiya Biotechnology Co., Ltd.
Category: otc | Type: HUMAN OTC DRUG LABEL
Date: 20250801

ACTIVE INGREDIENTS: ASCORBIC ACID 0.4 g/20 g; HYALURONIC ACID 0.24 g/20 g
INACTIVE INGREDIENTS: FERULIC ACID; UBIQUINONE; CHAMOMILE; CERAMIDE 3; GLYCOLIC ACID; RETINOIC ACID; .ALPHA.-TOCOPHEROL; CAFFEINE; NIACINAMIDE

PURPOSE

For Anti Ageing, Moisturizing, Antioxidant

INACTIVE INGREDIENT

Coenzyme Q10(CoQ10)
Ceramides
Niacinamide
Alpha hydroxy acids (AHAs)
Vitamin E
Caffeine
Retinoids
Ferulic acid
Chamomile

Warning.
1、For external use only, avoid contact with eyes when used
2、Keep out of reach of children

INDICATIONS AND USAGE

Reduces the appearance of dark circles, eye bags and wrinkles-Improves elasticity, firmness and skin resilience -Rejuvenates dark eye circles -Reduces under eye bags and puffiness

DOSAGE AND ADMINISTRATION

Before each use, press the top button of the essence pen 1-2 times. Gently roll and massage the area around your eyes with the essence pen until the essence is fully absorbed

KEEP OUT OF REACH OF CHILDREN SECTION

ACTIVE INGREDIENT

Hyaluronic acid 1.2%
Vitamin C 2%

PACKAGE LABEL

Active Ingredients
Hyaluronic acid 1.2%
Vitamin C 2%
Uses：
For Anti Ageing, Moisturizing, Antioxidant
The storage method：
Store sealed in a cool place and out of sunlight
Warning.
1、For external use only, avoid contact with eyes when used
2、Keep out of reach of children
Coenzyme Q10(CoQ10)
Ceramides
Niacinamide
Alpha hydroxy acids (AHAs)
Vitamin E
Caffeine
Retinoids
Ferulic acid
Chamomile